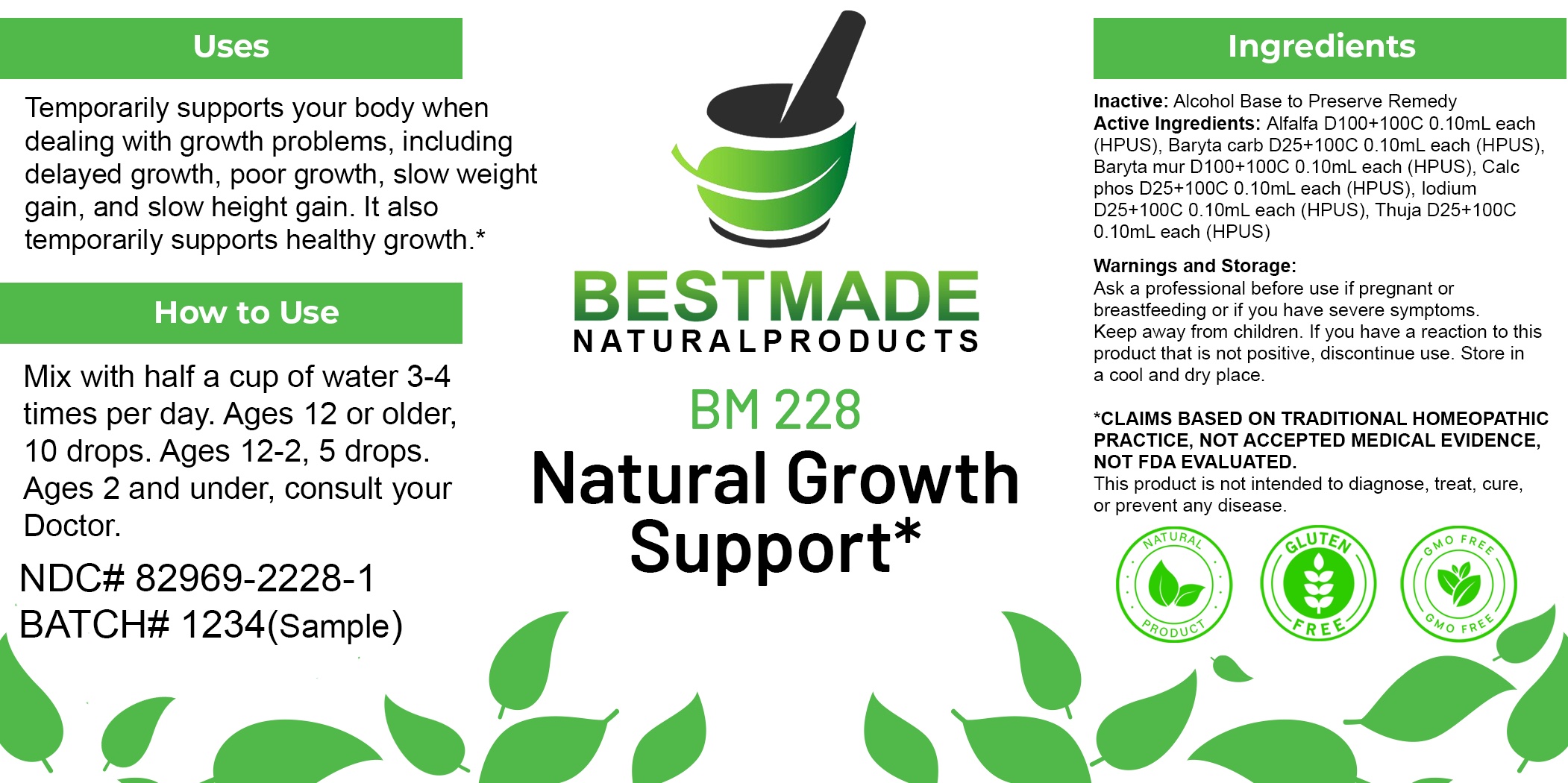 DRUG LABEL: Bestmade Natural Products BM228
NDC: 82969-2228 | Form: LIQUID
Manufacturer: Bestmade Natural Products
Category: homeopathic | Type: HUMAN OTC DRUG LABEL
Date: 20250304

ACTIVE INGREDIENTS: ALFALFA 30 [hp_C]/30 [hp_C]; TRIBASIC CALCIUM PHOSPHATE 30 [hp_C]/30 [hp_C]; BARIUM CARBONATE 30 [hp_C]/30 [hp_C]; IODINE 30 [hp_C]/30 [hp_C]; BARIUM CHLORIDE DIHYDRATE 30 [hp_C]/30 [hp_C]; THUJA OCCIDENTALIS LEAFY TWIG 30 [hp_C]/30 [hp_C]
INACTIVE INGREDIENTS: ALCOHOL 30 [hp_C]/30 [hp_C]

BM228

DOSAGE AND ADMINISTRATION

How to Use

Mix with half a cup of water 3-4 times per day. Ages 12 or older, 10 drops. Ages 12-2, 5 drops. Ages 2 and under, consult your Doctor.

Inactive:

Alcohol Base to Preserve Product

ACTIVE INGREDIENT

Active Ingredients: Alfalfa D100+100C 0.10mL each (HPUS), Baryta carb D25+100C 0.10mL each (HPUS), Baryta mur D100+100C 0.10mL each (HPUS), Calc phos D25+100C 0.10mL each (HPUS), Iodium D25+100C 0.10mL each (HPUS), Thuja D25+100C 0.10mL each (HPUS)

KEEP OUT OF REACH OF CHILDREN

Warnings and Storage:

Ask a professional before use if pregnant or breastfeeding or if you have severe symptoms.

Keep away from children. If you have a reaction to this product that is not positive, discontinue use. Store in a cool and dry place

*CLAIMS BASED ON TRADITIONAL HOMEOPATHIC PRACTICE, NOT ACCEPTED MEDICAL EVIDENCE NOT FDA EVALUATED.
This product is not intended to diagnose, treat, cure, or prevent any disease.

Warnings and Storage:

Ask a professional before use if pregnant or breastfeeding or if you have severe symptoms.

Keep away from children. If you have a reaction to this product that is not positive, discontinue use. Store in a cool and dry place

*CLAIMS BASED ON TRADITIONAL HOMEOPATHIC PRACTICE, NOT ACCEPTED MEDICAL EVIDENCE NOT FDA EVALUATED.
This product is not intended to diagnose, treat, cure, or prevent any disease.

Uses
Temporarily supports your body when dealing with growth problems, including delayed growth, poor growth, slow weight gain, and slow height gain. It also temporarily supports healthy growth.*

Uses
Temporarily supports your body when dealing with growth problems, including delayed growth, poor growth, slow weight gain, and slow height gain. It also temporarily supports healthy growth.*

Entire package label